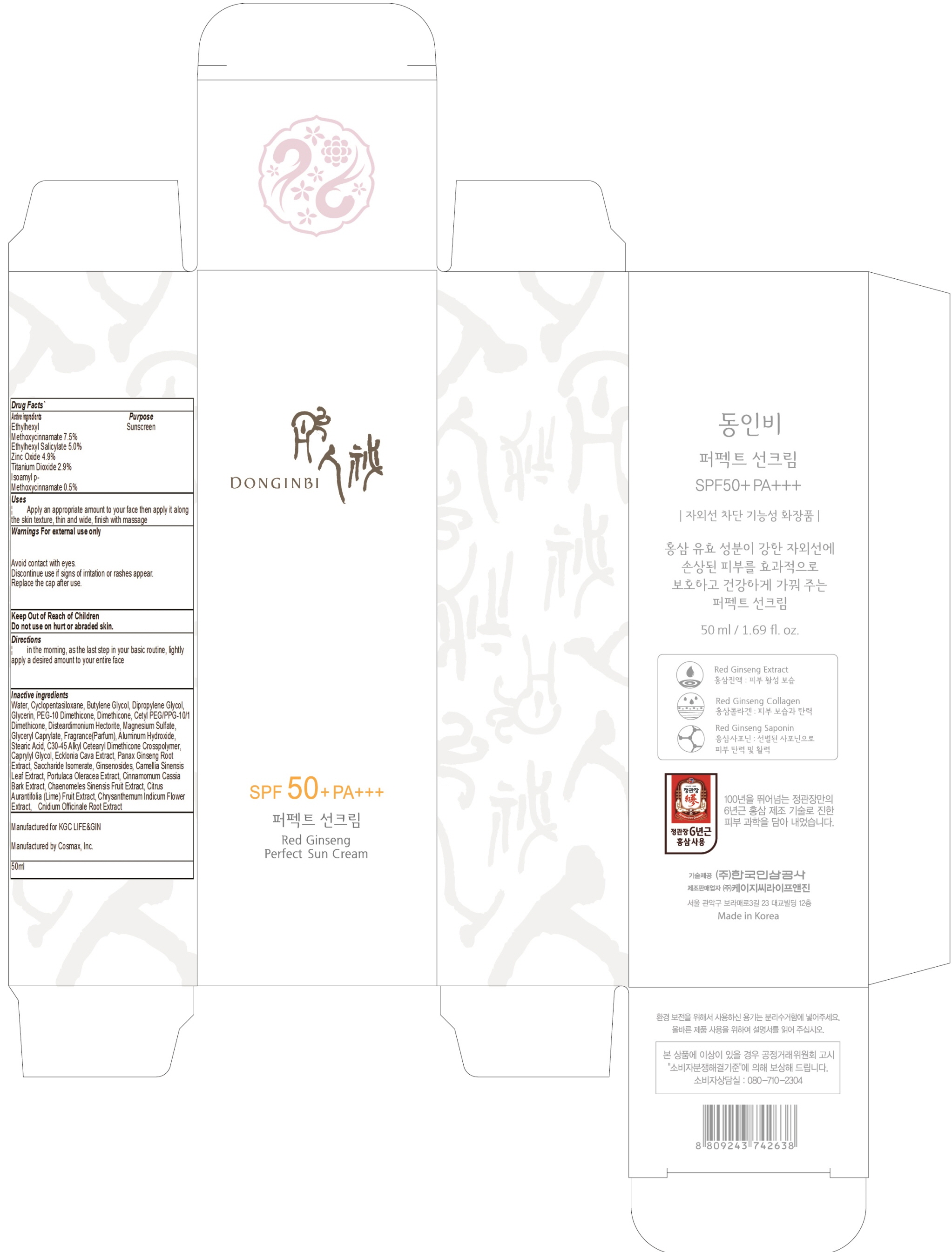 DRUG LABEL: DONGINBI Red Ginseng
NDC: 69640-4001 | Form: CREAM
Manufacturer: KGC LIFE&GIN
Category: otc | Type: HUMAN OTC DRUG LABEL
Date: 20170726

ACTIVE INGREDIENTS: Octinoxate 3.75 g/50 mL; Octisalate 2.5 g/50 mL; Zinc Oxide 2.45 g/50 mL; Titanium Dioxide 1.45 g/50 mL
INACTIVE INGREDIENTS: Water; Butylene Glycol

ACTIVE INGREDIENT

Active ingredients: Ethylhexyl Methoxycinnamate 7.5%, Ethylhexyl Salicylate 5.0%, Zinc Oxide 4.9%, Titanium Dioxide 2.9%

INACTIVE INGREDIENT

Inactive ingredients: Water, Cyclopentasiloxane, Butylene Glycol, Dipropylene Glycol, Glycerin, PEG-10 Dimethicone, Dimethicone, Cetyl PEG/PPG-10/1 Dimethicone, Disteardimonium Hectorite, Magnesium Sulfate, Isoamyl p-Methoxycinnamate, Glyceryl Caprylate, Fragrance(Parfum), Aluminum Hydroxide, Stearic Acid, C30-45 Alkyl Cetearyl Dimethicone Crosspolymer, Caprylyl Glycol, Ecklonia Cava Extract, Panax Ginseng Root Extract, Saccharide Isomerate, Ginsenosides, Camellia Sinensis Leaf Extract, Honey Extract, Portulaca Oleracea Extract, Cinnamomum Cassia Bark Extract, Chaenomeles Sinensis Fruit Extract, Citrus Aurantifolia (Lime) Fruit Extract, Chrysanthemum Indicum Flower Extract, Phenoxyethanol, Cnidium Officinale Root Extract, Methylparaben, Butylparaben, Ethylparaben, Isobutylparaben, Propylparaben

PURPOSE

Purpose: Sunscreen

WARNINGS

Warnings: For external use only. Avoid contact with eyes. Discontinue use if signs of irritation or rashes appear. Replace the cap after use.

Keep Out of Reach of Children: Do not use on hurt or abraded skin.

DESCRIPTION

Uses: Apply an appropriate amount to your face then apply it along the skin texture, thin and wide, finish with massage.

Directions: in the morning, as the last step in your basic routine, lightly apply a desired amount to your entire face.